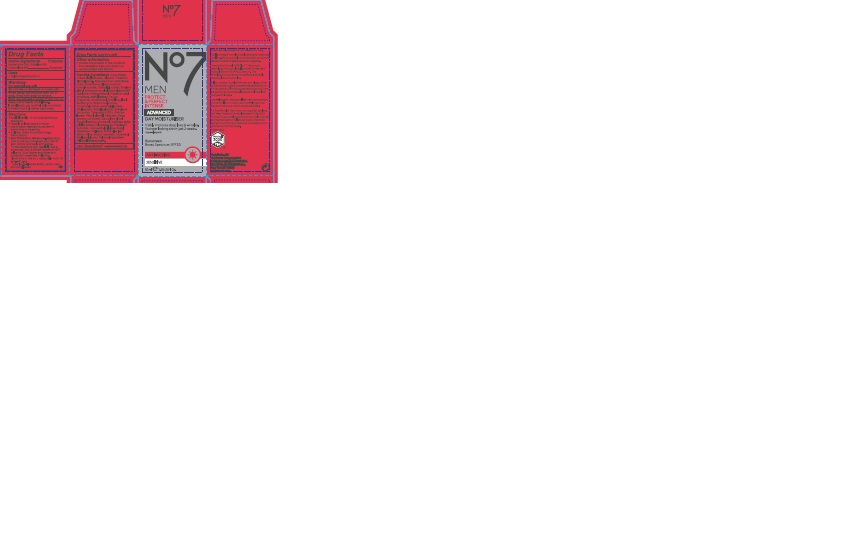 DRUG LABEL: No7 Men Protect and Perfect Intense Advanced Day Moisturiser SPF 30
NDC: 11489-108 | Form: CREAM
Manufacturer: BCM Ltd
Category: otc | Type: HUMAN OTC DRUG LABEL
Date: 20160922

ACTIVE INGREDIENTS: AVOBENZONE 1.5 g/50 g; OCTOCRYLENE 3.75 g/50 g; OCTISALATE 4 g/50 g
INACTIVE INGREDIENTS: WATER; GLYCERIN; DIMETHICONE; CETEARYL GLUCOSIDE; ALUMINUM STARCH OCTENYLSUCCINATE; TRIBEHENIN; POTASSIUM CETYL PHOSPHATE; AMMONIUM ACRYLOYLDIMETHYLTAURATE/VP COPOLYMER; PHENOXYETHANOL; SHEA BUTTER; BUTYLENE GLYCOL; METHYLPARABEN; DIMETHICONOL (40 CST); PROPYLENE GLYCOL; ASCORBYL GLUCOSIDE; DIPROPYLENE GLYCOL; XANTHAN GUM; ETHYLPARABEN; VITAMIN A PALMITATE; N-ACETYL DIPEPTIDE-1; MEDICAGO SATIVA LEAF; EDETATE SODIUM; TERT-BUTYL ALCOHOL; POLYSORBATE 20; CARBOMER 940; DIMETHYLMETHOXY CHROMANOL; POTASSIUM HYDROXIDE; ETHYLHEXYLGLYCERIN; PANAX GINSENG ROOT OIL; TOCOPHEROL; HYDROXYETHYL CELLULOSE (100 MPA.S AT 2%); MORUS ALBA LEAF; PALMITOYL TETRAPEPTIDE-7; SODIUM BENZOATE; PALMITOYL TRIPEPTIDE-1

No7 Men Protect and Perfect Intense Advanced Day Moisturiser Sunscreen Broad Spectrum SPF 30

Carton Active Ingredients Section

Active ingredients

Avobenzone 3%

Octisalate 5%

Octocrylene 8%

Uses

Uses - helps prevent sunburn

Warnings

For external use only

Do not use on damaged or broken skin

When using this product keep out of eyes. Rinse with water to remove.

Ask a doctor

Stop use and ask a doctor if rash occurs

Keep out of reach of children

If swallowed, get medical help or contact a Poison Control Center right away

Directions

Apply liberally 15 minutes before sun exposure

reapply at least every 2 hours

use a water resistant sunscreen if swimming or sweating

children under 6 months of age: Ask a doctor

Sun Protection Measures. Spending time in the sun increases your risk of skin cancer and early skin aging.

To decrease this risk, regularly use a sunscreen with a Broad Spectrum SPF value of 15 or higher and other sun protection measures including:

Limit time in the sun, especially from 10 a.m - 2 p.m.

wear long-sleeved shirts,pants,hats and sunglasses.

Storage

Other information

Protect the product in this container from excessive heat and direct sun

Avoid contact with fabrics

Inactive ingredients

Aqua(Water), C12-15 alkyl benzoate, Glycerin, Tribehenin, Alcohol denat., Dimethicone, Aluminum starch octenylsuccinate, Cetearyl glucoside, Butyrospermum parkii (Shea) butter, Butylene glycol, Ammonium acryloyldimethyltaurate/VP copolymer, Phenoxyethanol, Potassium cetyl phosphate, Methylparaben, Parfum(Fragrance), Dimethiconol, Propylene glycol,Xanthan gum, Sodium hyaluronate, Tocopheryl acetate, Ascorbyl glucoside, Ethylparaben, Retinyl palmitate, Hydrolyzed rice protein, Tetrasodium EDTA, Sorbitan laurate, T-butyl alcohol, Carbomer, Panax ginseng root extract, Dipropylene glycol, Dimethylmethoxy chromanol, Medicago sativa (Alfalfa) extract, Polysorbate 20, Potassium hydroxide, Hydroxyethylcellulose, Acetyl dipeptide-1 cetyl ester, Morus alba leaf extract, Silica, Sodium benzoate, Tocopherol, Ethylhexylglycerin, Palmitoyl tripeptide-1, Palmitoyl tetrapeptide-7

PATIENT COUNSELING INFORMATION

Made in the UK

The Boots Company PLC Nottingham England NG2 3AA

Dist. by Boots Retail USA Inc. New York NY 10005

www.boots.com

Description

No7 Men Protect and Perfect Intense Advanced Day Moisturiser Sunscreen Broad Spectrum SPF 30

Visibly improves deep lines and wrinkles

Younger looking skin in just 2 weeks.

Advanced daily protection formulated for men.

This lightweight formula is easily absorbed, even over facial hair. Working to help boost the skin's protective barrier and defend against premature ageing.

Powered by Matrixyl 3000 Plus TM, the unique technology from our clinically proven Protect and Perfect Intense ADVANCED serum. This formulation is now even more effective at visibly reducing lines and wrinkles.

It also contains Double Defence technology, which combined with the added Sunscreen Broad Spectrum SPF30, gives No7's most advanced protection from the sun and environmental stress to help skin look younger for longer.

Hypoallergenic: Because all skin can have sensitive moments all our products are hypo-allergenic so they are kind to even the most sensitive skin.

For Best Results: Use every morning after applying No7 Men Protect and Perfect Intense Advanced Serum. Pump a small amount into your palm and rub your hands together to leave an even amount on each. Smooth into your face and neck paying more attention to the drier areas.